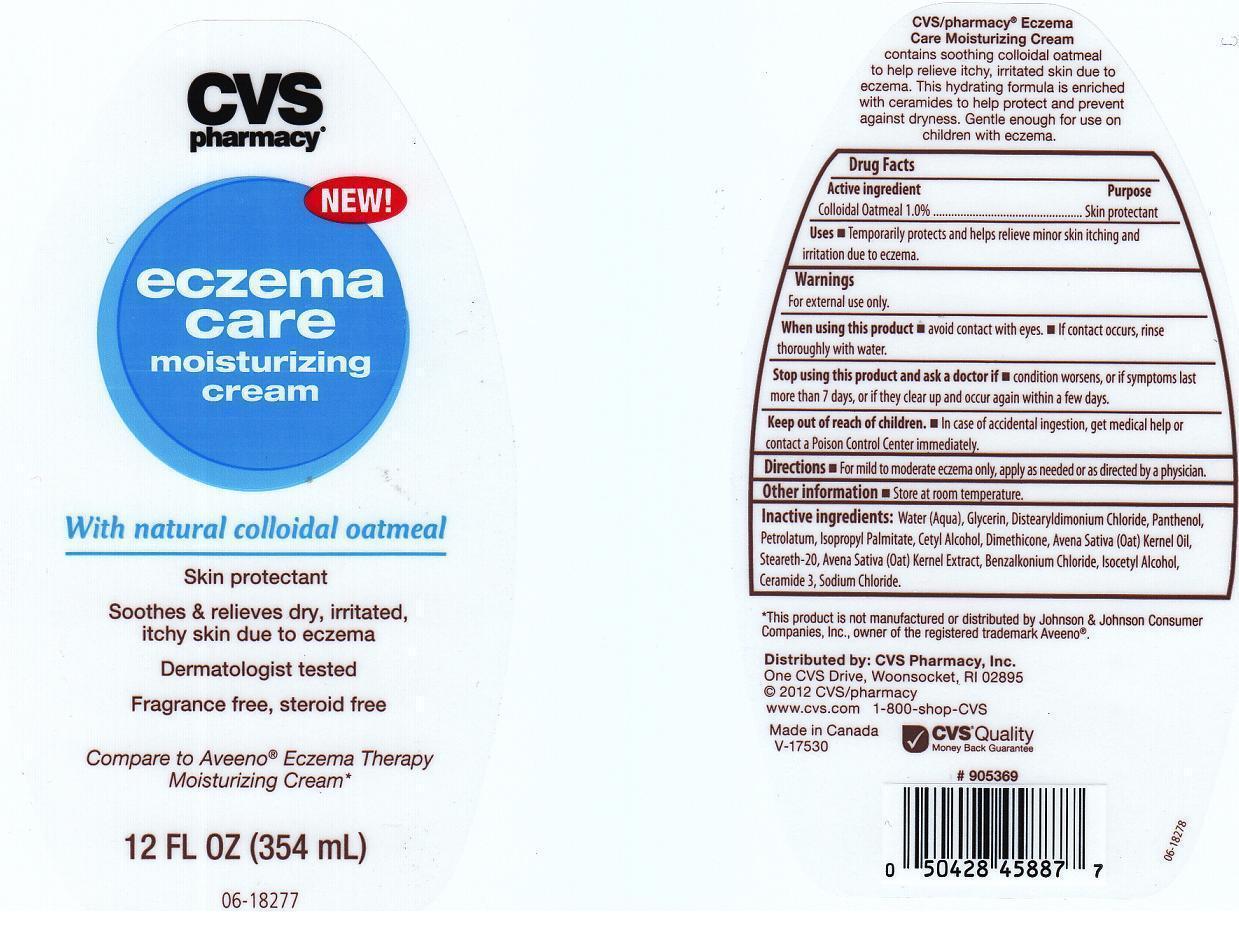 DRUG LABEL: ECZEMA CARE
NDC: 59779-355 | Form: LOTION
Manufacturer: CVS PHARMACY
Category: otc | Type: HUMAN OTC DRUG LABEL
Date: 20181112

ACTIVE INGREDIENTS: OATMEAL 10 mg/1 mL
INACTIVE INGREDIENTS: WATER; GLYCERIN; DISTEARYLDIMONIUM CHLORIDE; PANTHENOL; PETROLATUM; ISOPROPYL PALMITATE; CETYL ALCOHOL; DIMETHICONE; OAT KERNEL OIL; STEARETH-20; OAT; BENZALKONIUM CHLORIDE; ISOCETYL ALCOHOL; CERAMIDE 3; SODIUM CHLORIDE

DRUG FACTS

ACTIVE INGREDIENT

COLLOIDAL OATMEAL 1.0%

PURPOSE

SKIN PROTECTANT

USES

TEMPORARILY PROTECTS AND HELPS RELIEVE MINOR SKIN ITCHING AND IRRITATION DUE TO ECZEMA.

WARNINGS

FOR EXTERNAL USE ONLY.

WHEN USING THIS PRODUCT

AVOID CONTACT WITH EYES. IF CONTACT OCCURS, RINSE THOROUGHLY WITH WATER.

STOP USING THIS PRODUCT AND ASK A DOCTOR IF

CONDITION WORSENS, OR IF SYMPTOMS LAST MORE THAN 7 DAYS, OR IF THEY CLEAR UP AND OCCUR AGAIN WITHIN A FEW DAYS.

KEEP OUT OF REACH OF CHILDREN

IN CASE OF ACCIDENTAL INGESTION, GET MEDICAL HELP OR CONTACT A POISON CONTROL CENTER IMMEDIATELY.

DIRECTIONS

FOR MILD TO MODERATE ECZEMA ONLY, APPLY AS NEEDED OR AS DIRECTED BY A PHYSICIAN.

OTHER INFORMATION

STORE AT ROOM TEMPERATURE.

INACTIVE INGREDIENTS:

WATER (AQUA), GLYCERIN, DISTEARYLDIMONIUM CHLORIDE, PANTHENOL, PETROLATUM, ISOPROPYL PALMITATE, CETYL ALCOHOL, DIMETHICONE, AVENA SATIVA (OAT) KERNEL OIL, STEARETH-20, AVENA SATIVA (OAT) KERNEL EXTRACT, BENZALKONIUM CHLORIDE, ISOCETYL ALCOHOL, CERAMIDE 3, SODIUM CHLORIDE.